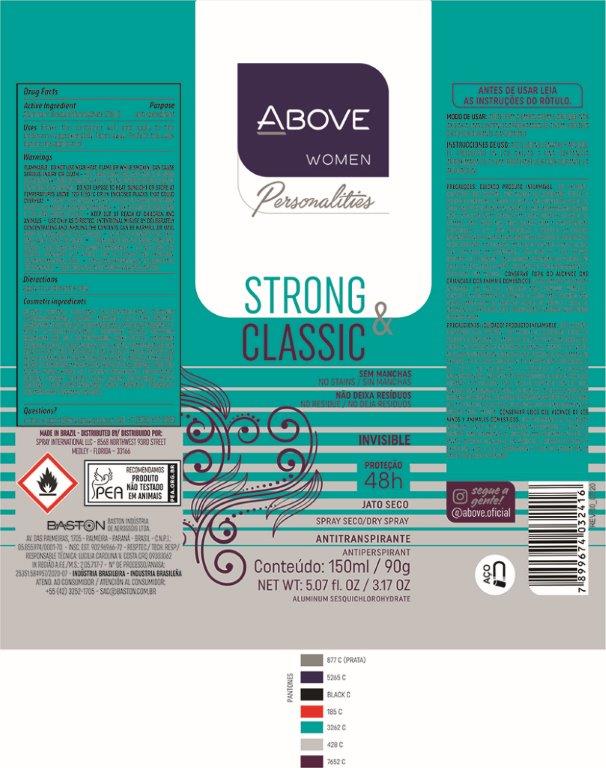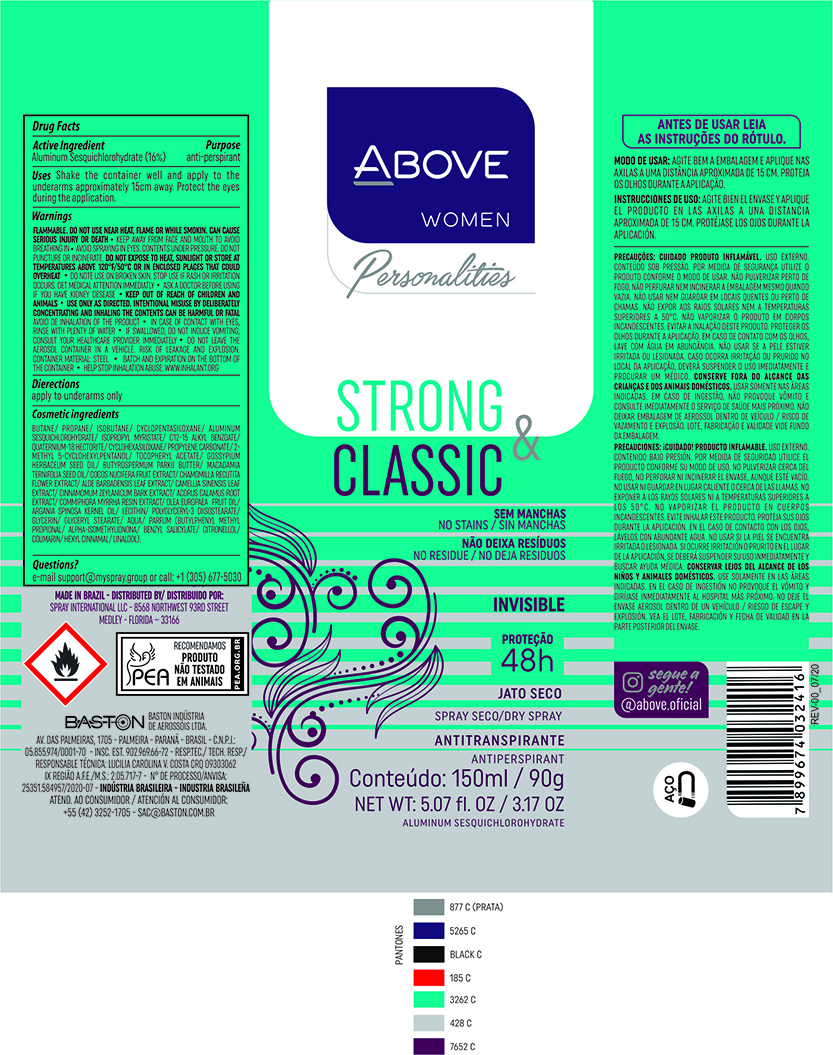 DRUG LABEL: ANTIPERSPIRANT ABOVE PERSONALITIES STRONG E CLASSIC
NDC: 73306-1122 | Form: AEROSOL, SPRAY
Manufacturer: BASTON INDUSTRIA DE AEROSSÓIS LTDA
Category: otc | Type: HUMAN OTC DRUG LABEL
Date: 20241226

ACTIVE INGREDIENTS: ALUMINUM SESQUICHLOROHYDRATE 16 g/100 g
INACTIVE INGREDIENTS: GLYCERYL MONOSTEARATE; WATER; SHEA BUTTER; CINNAMON BARK OIL; CHAMOMILE; ISOBUTANE; DISTEARDIMONIUM HECTORITE; COCONUT; LECITHIN, SOYBEAN; PROPANE; CYCLOMETHICONE 5; GLYCERIN; ISOPROPYL MYRISTATE; ALOE VERA LEAF; ALKYL (C12-15) BENZOATE; MACADAMIA OIL; PROPYLENE CARBONATE; ARGAN OIL; .ALPHA.-TOCOPHEROL ACETATE; LEVANT COTTON SEED; MYRRH OIL; GREEN TEA LEAF; BUTANE; DIMETHICONE; ACORUS CALAMUS ROOT; POLYGLYCERYL-3 DIISOSTEARATE; 2-METHYL 5-CYCLOHEXYLPENTANOL

ANTIPERSPIRANT ABOVE PERSONALITIES STRONG E CLASSIC

ACTIVE INGREDIENT

ALUMINUM SESQUICHLOROHYDRATE 16%

PURPOSE

Antiperspirant

INDICATIONS AND USAGE

Uses - reduces underarm wetness

DOSAGE AND ADMINISTRATION

Directions -Apply to underarms only

INACTIVE INGREDIENT

BUTANE/PROPANE/ISOBUTANE/CYCLOPENTASILOXANE/ALUMINUM SESQUICHLOROHYDRATE/ISOPROPYL MYRISTATE/C12-15 ALKYL BENZOATE/QUATERNIUM-18 HECTORITE/CYCLOHEXASILOXANE/PROPYLENE CARBONATE/2-METHYL 5-CYCLOHEXYLPENTANOL/TOCOPHERYL ACETATE/GOSSYPIUM HERBACEUM SEED OIL/
BUTYROSPERMUM PARKII BUTTER/MACADAMIA TERNIFOLIA SEED OIL/COCOS NUCIFERA FRUIT EXTRACT/CHAMOMILLA RECUTITA FLOWER EXTRACT/ALOE BARBADENSIS LEAF EXTRACT/CAMELLIA SINENSIS LEAF EXTRACT/CINNAMOMUM ZEYLANICUM BARK EXTRACT/ACORUS CALAMUS ROOT EXTRACT/COMMIPHORA MYRRHA RESIN EXTRACT/OLEA EUROPAEA FRUIT OIL/ARGANIA SPINOSA KERNEL OIL/LECITHIN/POLYGLYCERYL-3 DIISOSTEARATE/GLYCERIN/GLYCERYL STEARATE/AQUA/PARFUM(BUTYLPHENYL METHYL PROPIONAL/ALPHA-ISOMETHYLIONONA/
BENZYL SALICYLATE/CITRONELLOL/COUMARIN/HEXYL CINNAMAL/LINALOOL).

QUESTIONS

e-mail: sac @baston.com.br or call: +1(305)677-5030

Keep Out Of Reach Of Children

WARNINGS AND PRECAUTIONS

•Flammable until fully dry. Do not use near heat, Flame or while smoking. Can cause serious
injury or deat•Keep away from face and mouth to avoid breathing in•Avoid spraying in
eyes•Contents under pressure•Do not puncture or incinerate•Do not expose to heat or store at
temperatures above 120 ºF/50 ºC or in enclosed places that could overheat•Do not use on
broken skin•Stop use if rash or irritation occurs•Ask a doctor before using if you have kidney
disease•USE ONLY AS DIRECTED•INTENTIONAL MISUSE BY DELIBERATELY
CONCENTRATING AND INHALING THE CONTENTS CAN BE HARMFUL OR
FATAL•Avoid de inhalation of the product.